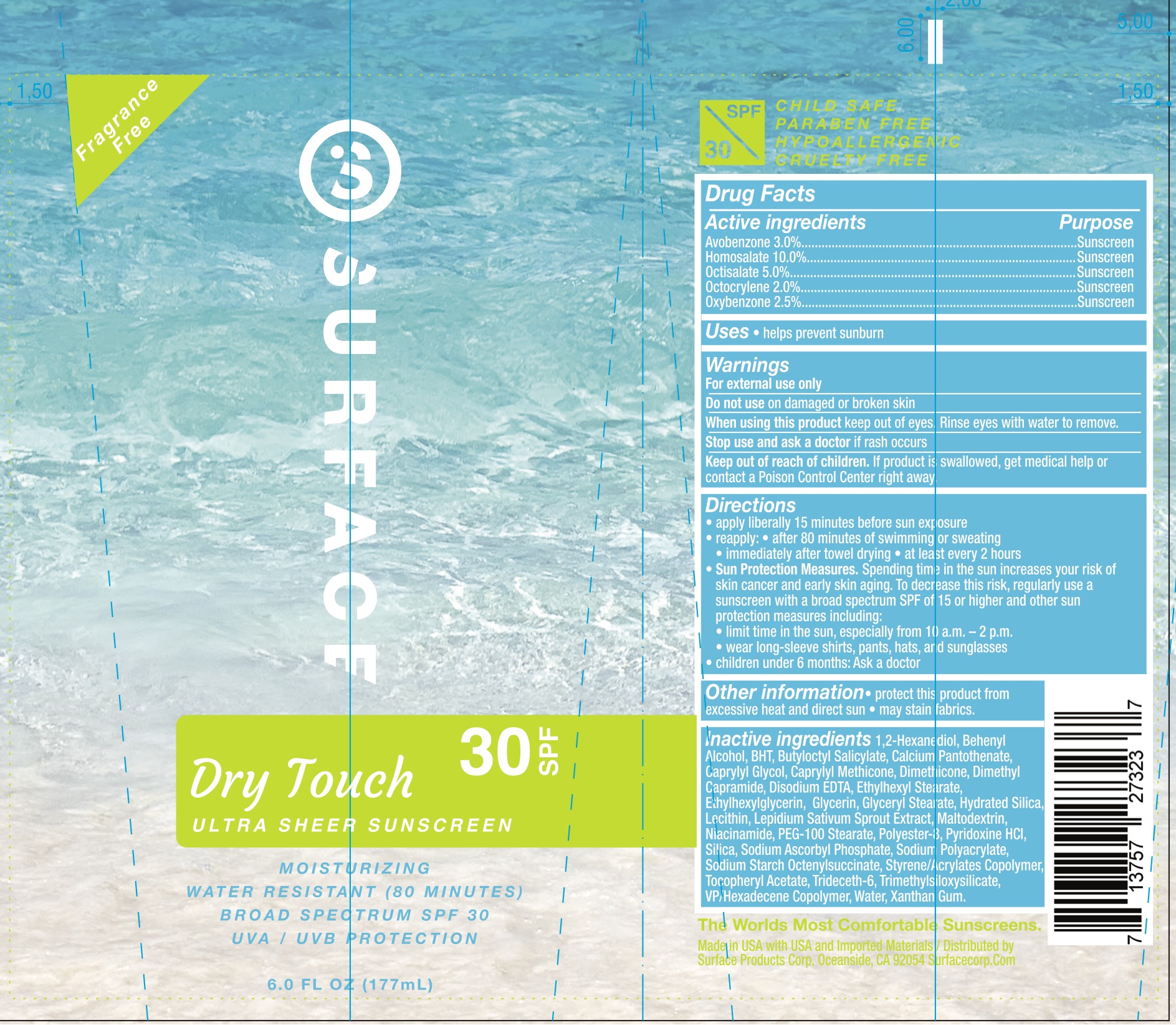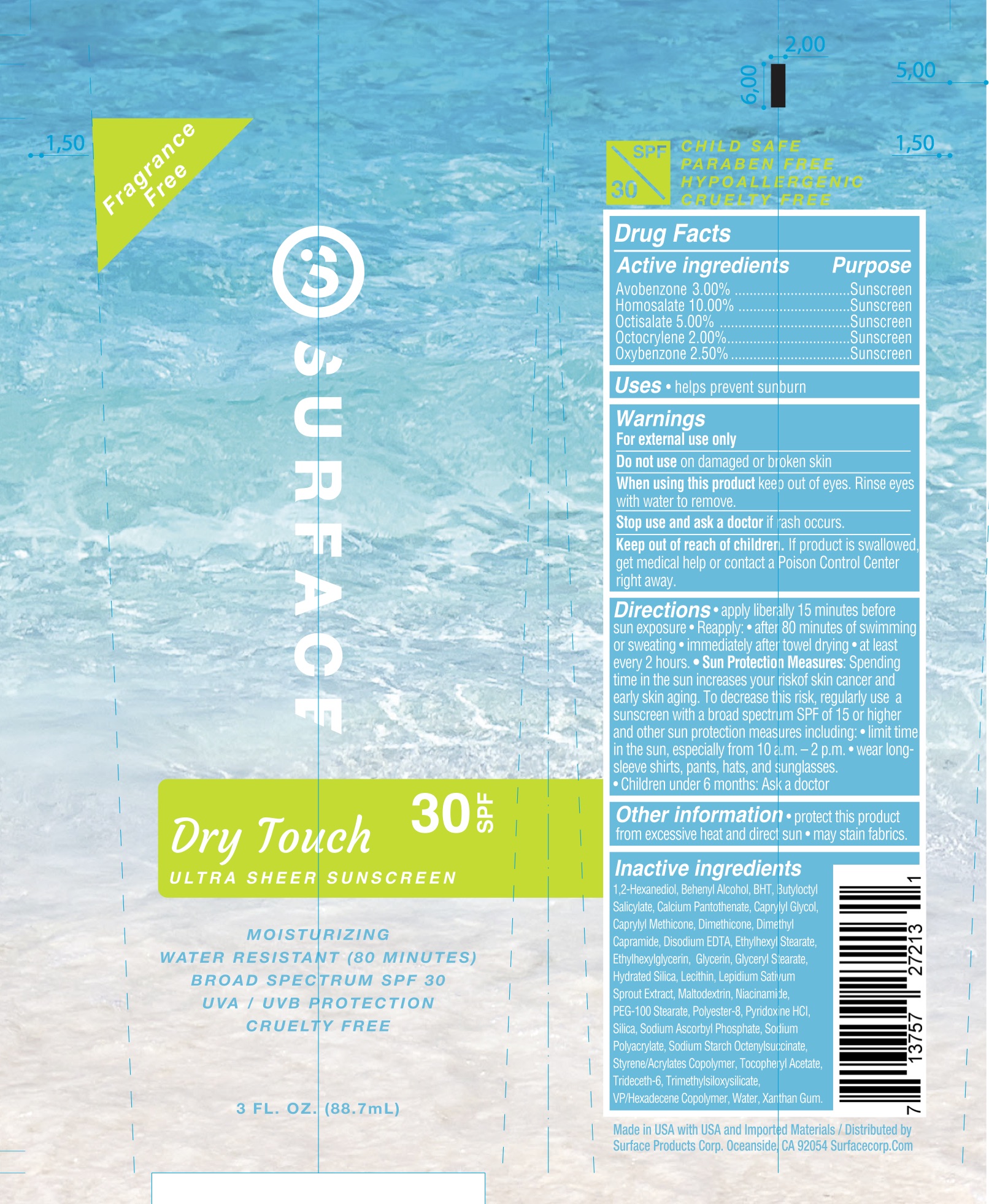 DRUG LABEL: Surface Sun Dry Touch SPF 30 Sunscreen
NDC: 72344-009 | Form: LOTION
Manufacturer: Surface Products Corp
Category: otc | Type: HUMAN OTC DRUG LABEL
Date: 20180530

ACTIVE INGREDIENTS: AVOBENZONE 3 g/100 mL; HOMOSALATE 10 g/100 mL; OCTISALATE 5 g/100 mL; OCTOCRYLENE 2 g/100 mL; OXYBENZONE 2.5 g/100 mL
INACTIVE INGREDIENTS: VINYLPYRROLIDONE/HEXADECENE COPOLYMER; SODIUM POLYACRYLATE (8000 MW); TRIDECETH-6; XANTHAN GUM; ACRYLIC ACID; TRIMETHYLSILOXYSILICATE (M/Q 0.66); EDETATE DISODIUM; WATER; PROPYLENE GLYCOL; HYDRATED SILICA; BUTYLOCTYL SALICYLATE; 1,2-HEXANEDIOL; DIMETHYL CAPRAMIDE; ETHYLHEXYL STEARATE; ETHYLHEXYLGLYCERIN; BUTYLATED HYDROXYTOLUENE; PEG-100 STEARATE; DIMETHICONE; GLYCERYL MONOSTEARATE; BENZYL ALCOHOL; POLYESTER-8 (1400 MW, CYANODIPHENYLPROPENOYL CAPPED); CAPRYLYL TRISILOXANE; ALLANTOIN CALCIUM PANTOTHENATE; CAPRYLYL GLYCOL; GLYCERIN; EGG PHOSPHOLIPIDS; GARDEN CRESS SPROUT; MALTODEXTRIN; NIACINAMIDE; SILICON DIOXIDE; SODIUM ASCORBYL PHOSPHATE; ALUMINUM STARCH OCTENYLSUCCINATE; PYRIDOXINE HYDROCHLORIDE; .ALPHA.-TOCOPHEROL ACETATE

Active Ingredients

Avobenzone 3%, Homosalate 10%, Octisalate 5%, Octocrylene 2%, Oxybenzone 2.5%

Purpose

Sunscreen

Use

Helps prevent sunburn.

Warnings

For external use only.

Do not use on damaged or broken skin. When using this product keep out of eyes. Rinse eyes with water to remove. Stop use and ask a doctor if rash occurs.

Keep Out of Reach of Children.

If product is swallowed, get medical help or contact a Poison Control Center right away.

Directions

Apply liberally 15 minutes before sun exposure. Reapply:

- after 80 minutes of swimming or sweating
- immediately after towel drying
- at least every 2 hours.

Sun Protection Measures: Spending time in the sun increases your risk of skin cancer and early skin aging. To decrease this risk, regularly use a sunscreen with a broad spectrum SPF of 15 or higher and other sun protection measures including:

- Limit time in the sun, especially from 10 a.m. - 2 p.m.
- Wear long-sleeved shirts, pants, hats, and sunglasses.

Children under 6 months: ask a doctor.

Inactive Ingredients

1,2-Hexanediol, Behenyl Alcohol, BHT, Butyloctyl Salicylate, Calcium Pantothenate, Caprylyl Glycol, Caprylyl Methicone, Dimethicone, Dimethyl Capramide, Disodium EDTA, Ethylhexyl Stearate, Ethylhexylglycerin, Glycerin, Glyceryl Stearate, Hydrated Silica, Lecithin, Lepidium Sativum Sprout Extract, Maltodextrin, Niacinamide, PEG-100 Stearate, Polyester-8, Pyridoxine HCl, Silica, Sodium Ascorbyl Phosphate, Sodium Polyacrylate, Sodium Starch Octenylsuccinate, Styrene/Acrylates Copolymer, Tocopheryl Acetate, Trideceth-6, Trimethylsiloxysilicate, VP/Hexadecene Copolymer, Water, Xanthan Gum.